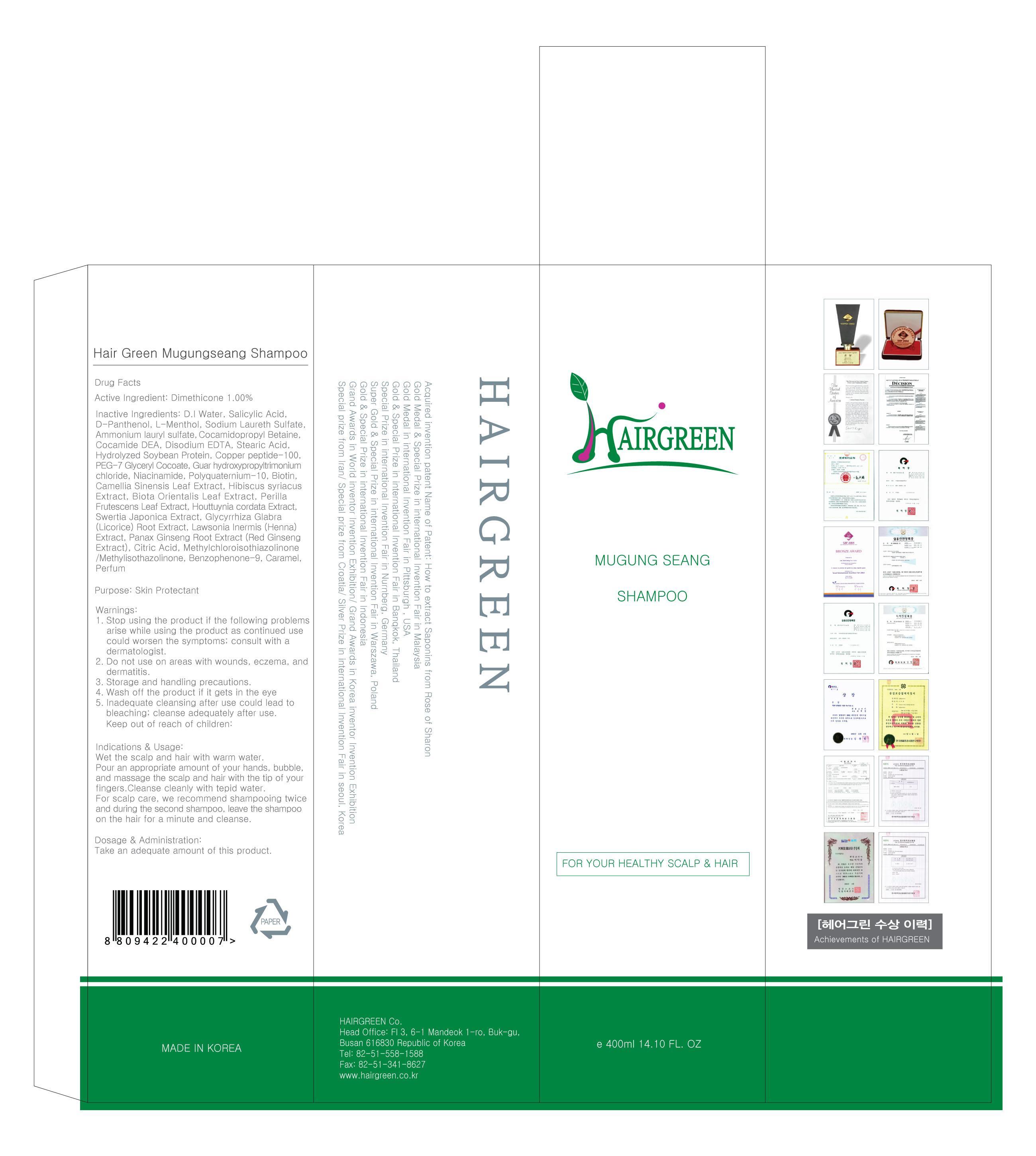 DRUG LABEL: Hair Green Mugungseang
NDC: 69773-010 | Form: SHAMPOO
Manufacturer: HAIRGREEN
Category: otc | Type: HUMAN OTC DRUG LABEL
Date: 20150506

ACTIVE INGREDIENTS: Dimethicone 4 mg/400 mL
INACTIVE INGREDIENTS: Water; Salicylic Acid

ACTIVE INGREDIENT

Active Ingredient: Dimethicone 1.00%

INACTIVE INGREDIENT

Inactive Ingredients: D.I Water, Salicylic Acid, D-Panthenol, L-Menthol, Sodium Laureth Sulfate, Ammonium lauryl sulfate, Cocamidopropyl Betaine, Cocamide DEA, Disodium EDTA, Stearic Acid, Hydrolyzed Soybean Protein, Copper peptide-100, PEG-7 Glyceryl Cocoate, Guar hydroxypropyltrimonium chloride, Niacinamide, Polyquaternium-10, Biotin, Camellia Sinensis Leaf Extract, Hibiscus syriacus Extract, Biota Orientalis Leaf Extract, Perilla Frutescens Leaf Extract, Houttuynia cordata Extract, Swertia Japonica Extract, Glycyrrhiza Glabra (Licorice) Root Extract, Lawsonia Inermis (Henna) Extract, Panax Ginseng Root Extract (Red Ginseng Extract), Citric Acid, Methylchloroisothiazolinone/Methylisothazolinone, Benzophenone-9, Caramel, Perfum

PURPOSE

Purpose: Skin Protectant

WARNINGS

Warnings: 1. Stop using the product if the following problems arise while using the product as continued use could worsen the symptoms; consult with a dermatologist. 2. Do not use on areas with wounds, eczema, and dermatitis. 3. Storage and handling precautions. 4. Wash off the product if it gets in the eye 5. Inadequate cleansing after use could lead to bleaching; cleanse adequately after use

KEEP OUT OF REACH OF CHILDREN

INDICATIONS & USAGE

Indications & Usage: Wet the scalp and hair with warm water. Pour an appropriate amount of your hands, bubble, and massage the scalp and hair with the tip of your fingers. Cleanse cleanly with tepid water. For scalp care, we recommend shampooing twice and during the second shampoo, leave the shampoo on the hair for a minute and cleanse.

DOSAGE & ADMINISTRATION

Dosage & Administration: Take an adequate amount of this product.